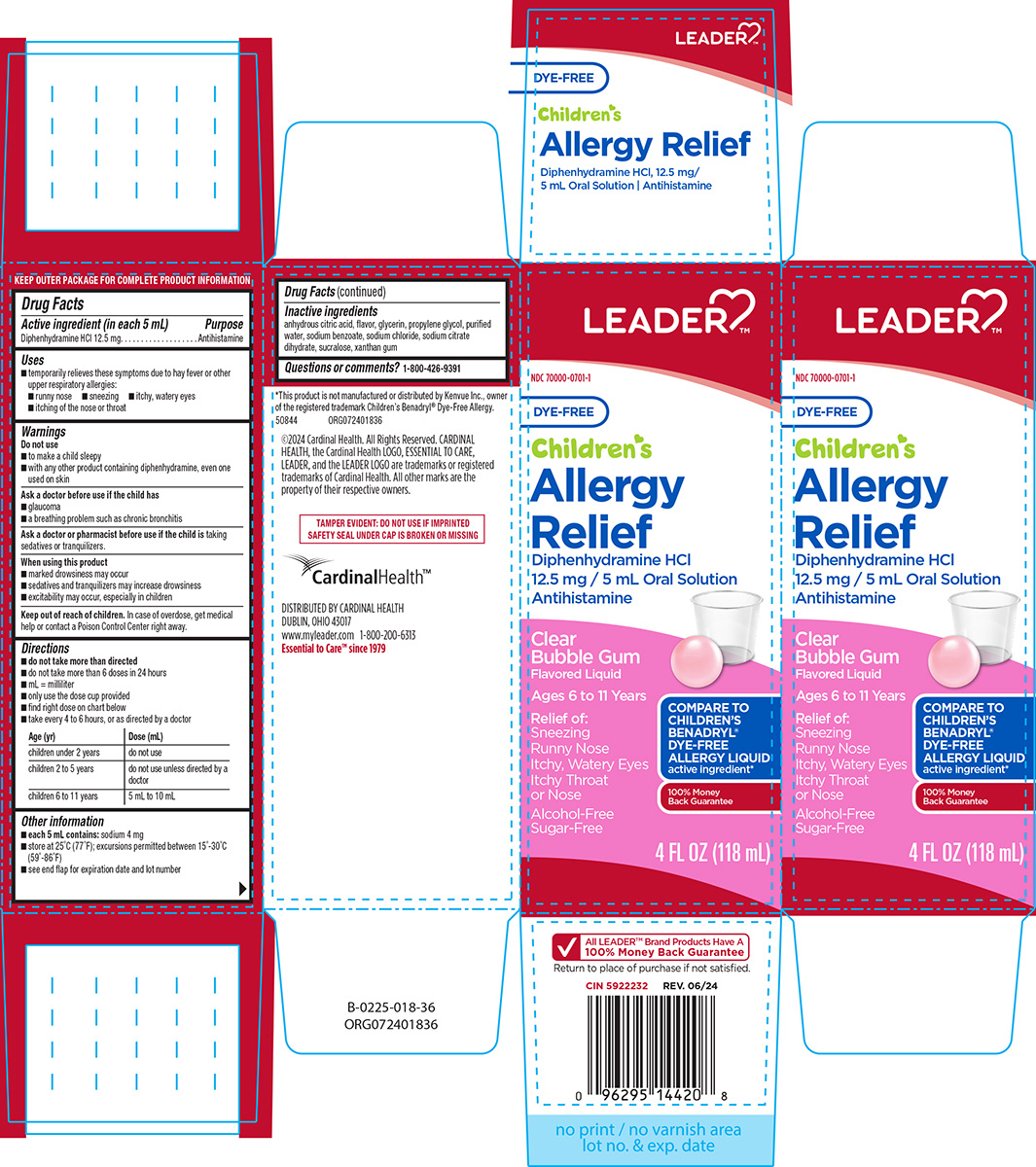 DRUG LABEL: Childrens Allergy Relief
NDC: 70000-0701 | Form: SOLUTION
Manufacturer: Cardinal Health 110, LLC. DBA Leader
Category: otc | Type: HUMAN OTC DRUG LABEL
Date: 20250428

ACTIVE INGREDIENTS: DIPHENHYDRAMINE HYDROCHLORIDE 12.5 mg/5 mL
INACTIVE INGREDIENTS: ANHYDROUS CITRIC ACID; GLYCERIN; PROPYLENE GLYCOL; WATER; SODIUM BENZOATE; SODIUM CHLORIDE; TRISODIUM CITRATE DIHYDRATE; SUCRALOSE; XANTHAN GUM

Leader 44-018

Active ingredient (in each 5 mL)

Diphenhydramine HCl 12.5 mg

Purpose

Antihistamine

Uses

- temporarily relieves these symptoms due to hay fever or other upper respiratory allergies:
  - runny nose
  - sneezing
  - itchy, watery eyes
  - itching of the nose or throat

Warnings

Do not use

- to make a child sleepy
- with any other product containing diphenhydramine, even one used on skin

Ask a doctor before use if the child has

- glaucoma
- a breathing problem such as chronic bronchitis

Ask a doctor or pharmacist before use if the child is

taking sedatives or tranquilizers.

When using this product

- marked drowsiness may occur
- sedatives and tranquilizers may increase drowsiness
- excitability may occur, especially in children

Keep out of reach of children.

In case of overdose, get medical help or contact a Poison Control Center right away.

Directions

- do not take more than directed
- do not take more than 6 doses in 24 hours
- mL = milliliter
- only use the dose cup provided
- find right dose on chart below
- take every 4 to 6 hours, or as directed by a doctor

Age (yr) | Dose (mL)
children under 2 years | do not use
children 2 to 5 years | do not use unless directed by a doctor
children 6 to 11 years | 5 mL to 10 mL

Other information

- each 5 mL contains: sodium 4 mg
- store at 25ºC (77ºF); excursions permitted between 15º-30ºC (59º-86ºF)
- see end flap for expiration date and lot number

Inactive ingredients

anhydrous citric acid, flavor, glycerin, propylene glycol, purified water, sodium benzoate, sodium chloride, sodium citrate dihydrate, sucralose, xanthan gum

Questions or comments?

1-800-426-9391

Principal Display Panel

LEADER™

NDC 70000-0701-1

DYE-FREE

Children's
Allergy
Relief
Diphenhydramine HCl
12.5 mg / 5 mL Oral Solution
Antihistamine

Clear
Bubble Gum
Flavored Liquid
Ages 6 to 11 Years
Relief of:
Sneezing
Runny Nose
Itchy, Watery Eyes
Itchy Throat
or Nose
Alcohol-Free
Sugar-Free

COMPARE TO
CHILDREN’S
BENADRYL®
DYE-FREE
ALLERGY LIQUID
active ingredient*

100% Money
Back Guarantee

4 FL OZ (118 mL)

*This product is not manufactured or distributed by Kenvue Inc., owner
of the registered trademark Children’s Benadryl® Dye-Free Allergy.
50844 ORG072401836

©2024 Cardinal Health. All Rights Reserved. CARDINAL
HEALTH, the Cardinal Health LOGO, ESSENTIAL TO CARE,
LEADER, and the LEADER LOGO are trademarks or registered
trademarks of Cardinal Health. All other marks are the
property of their respective owners.

TAMPER EVIDENT: DO NOT USE IF IMPRINTED
SAFETY SEAL UNDER CAP IS BROKEN OR MISSING

CardinalHealth™

DISTRIBUTED BY CARDINAL HEALTH
DUBLIN, OHIO 43017
www.myleader.com 1-800-200-6313
Essential to Care™ since 1979

LEADER 44-018